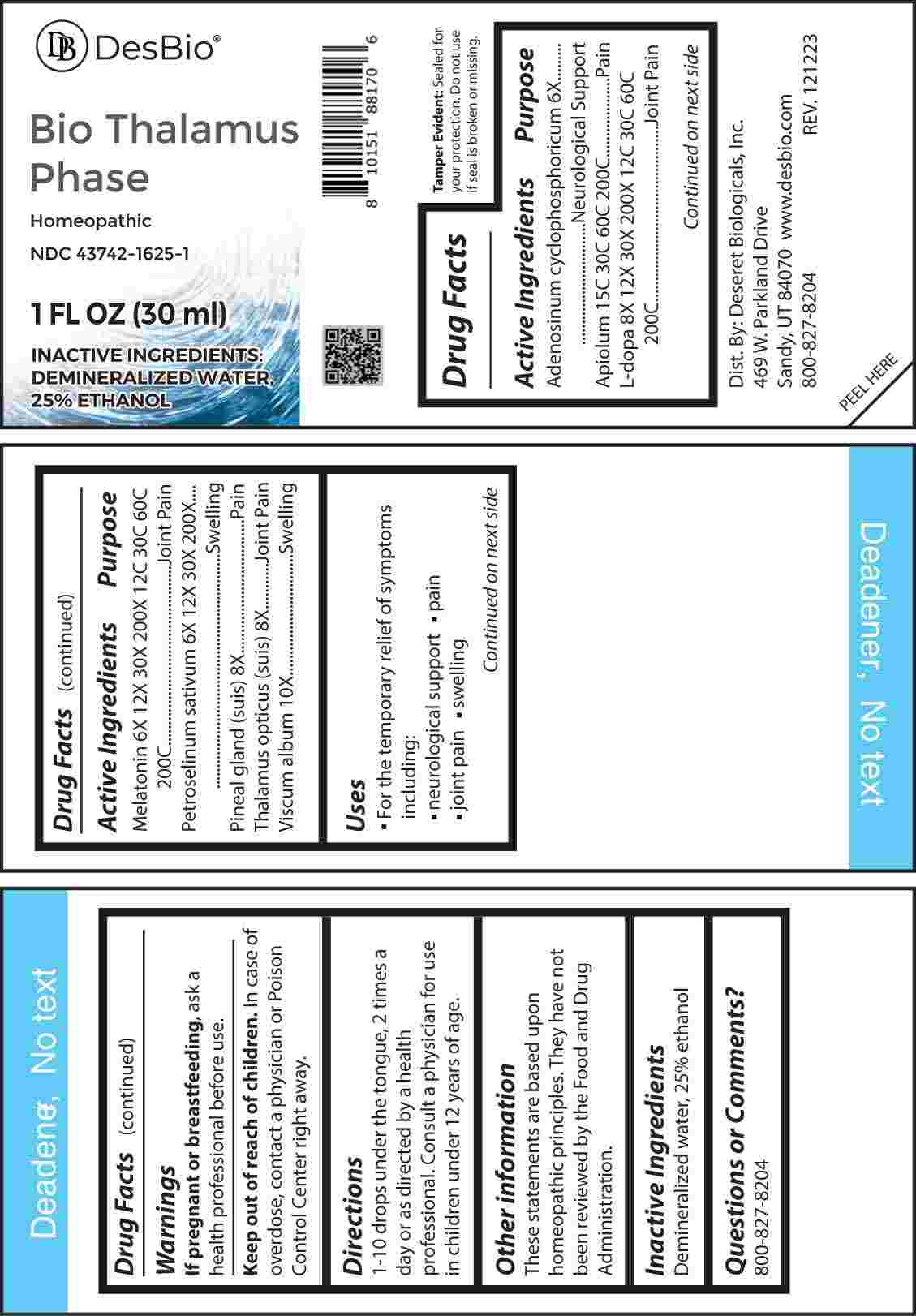 DRUG LABEL: Bio Thalamus Phase
NDC: 43742-1625 | Form: LIQUID
Manufacturer: Deseret Biologicals, Inc.
Category: homeopathic | Type: HUMAN OTC DRUG LABEL
Date: 20240315

ACTIVE INGREDIENTS: ADENOSINE CYCLIC PHOSPHATE 6 [hp_X]/1 mL; PETROSELINUM CRISPUM WHOLE 6 [hp_X]/1 mL; MELATONIN 6 [hp_X]/1 mL; SUS SCROFA PINEAL GLAND 8 [hp_X]/1 mL; SUS SCROFA THALAMUS LATERAL GENICULATE NUCLEUS 8 [hp_X]/1 mL; LEVODOPA 8 [hp_X]/1 mL; VISCUM ALBUM FRUITING TOP 10 [hp_X]/1 mL; APIOLE (PARSLEY) 15 [hp_C]/1 mL
INACTIVE INGREDIENTS: WATER; ALCOHOL

DRUG FACTS:

ACTIVE INGREDIENTS:

Adenosinum Cyclophosphoricum 6X, Apiolum 15C, 30C, 60C, 200C, L-Dopa 8X, 12X, 30X, 200X, 12C, 30C, 60C, 200C, Melatonin 6X, 12X, 30X, 200X, 12C, 30C, 60C, 200C, Petroselinum Sativum 6X, 12X, 30X, 200X, Pineal (Suis) 8X, Thalamus Opticus (Suis) 8X, Viscum Album 10X.

PURPOSE:

Adenosinum Cyclophosphoricum – Neurological Support, Apiolum - Pain, L-Dopa – Joint Pain, Melatonin – Joint Pain, Petroselinum Sativum - Swelling, Pineal (Suis) - Pain, Thalamus Opticus (Suis) – Joint Pain, Viscum Album - Swelling

USES:

• For the temporary relief of symptoms including:

• neurological support • pain • joint pain • swelling

These statements are based upon homeopathic principles. They have not been reviewed by the Food and Drug Administration.

WARNINGS:

If pregnant or breast-feeding, ask a health professional before use.

Keep out of reach of children. In case of overdose, contact a physician or Poison Control Center right away.

Tamper Evident: Sealed for your protection. Do not use if seal is broken or missing.

KEEP OUT OF REACH OF CHILDREN:

In case of overdose, contact a physician or Poison Control Center right away.

DIRECTIONS:

1-10 drops under the tongue, 2 times a day or as directed by a health professional. Consult a physician for use in children under 12 years of age.

INACTIVE INGREDIENTS:

Demineralized water, 25% ethanol

QUESTIONS:

Dist. By: Deseret Biologicals, Inc.

469 W. Parkland Drive

Sandy, UT 84070

www.desbio.com

800-827-8204

PACKAGE LABEL DISPLAY:

Des Bio

Bio Thalamus Phase

Homeopathic

NDC 43742-1625-1

1 FL OZ (30 ml)